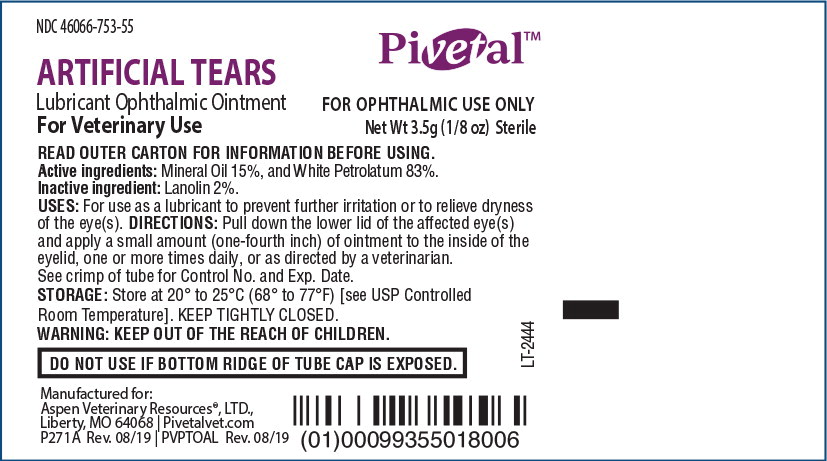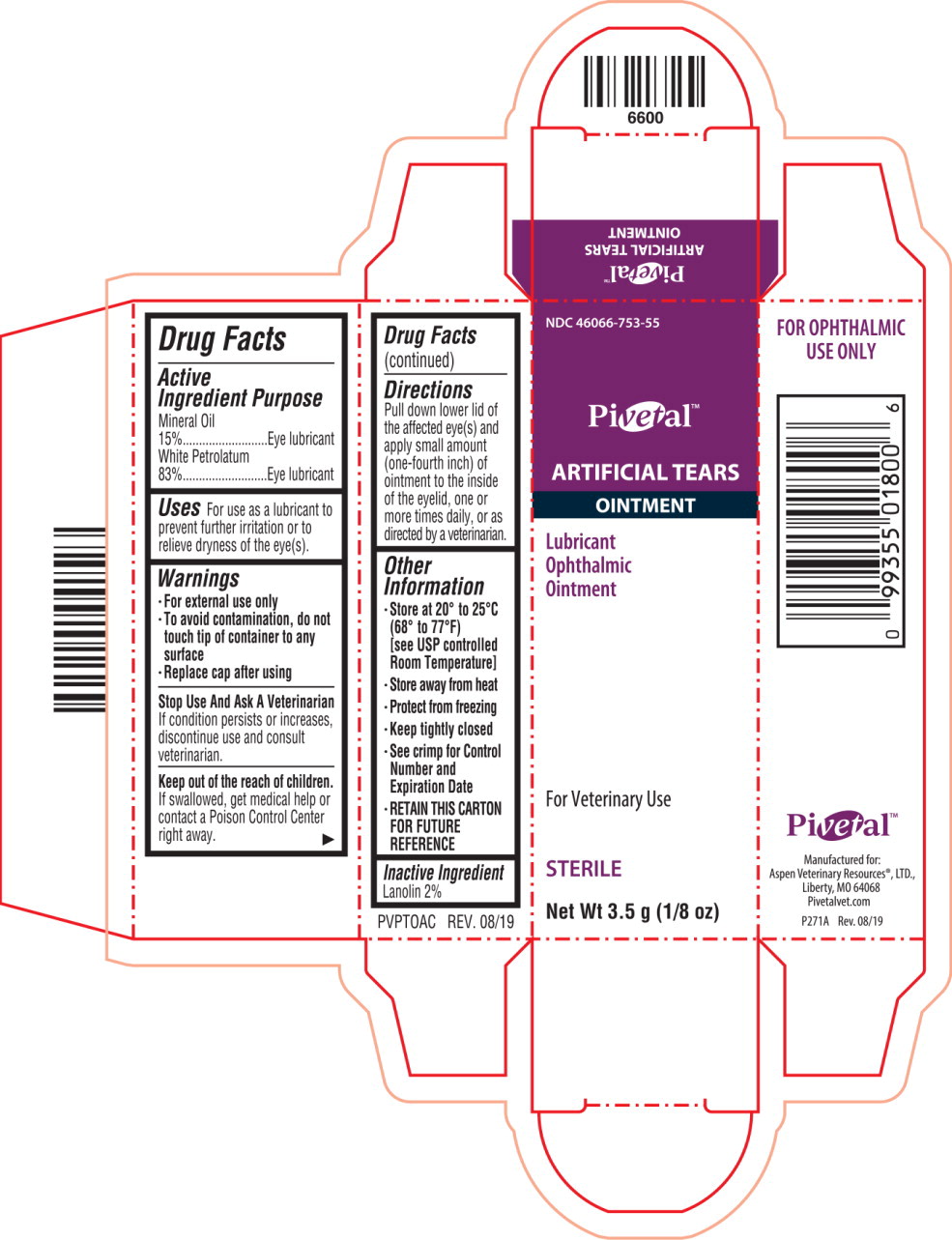 DRUG LABEL: ARTIFICIAL TEARS
NDC: 46066-753 | Form: OINTMENT
Manufacturer: Aspen Veterinary Resources
Category: animal | Type: OTC ANIMAL DRUG LABEL
Date: 20220208

ACTIVE INGREDIENTS: Mineral Oil 150 mg/1 g; Petrolatum 830 mg/1 g
INACTIVE INGREDIENTS: Lanolin

Drug Facts

Active Ingredient

Mineral Oil 15%

White Petrolatum 83%

Purpose

Eye lubricant

Eye lubricant

Uses

For use as a lubricant to prevent further irritation or to relieve dryness of the eye(s).

Warnings

- For external use only
- To avoid contamination, do not touch tip of container to any surface
- Replace cap after using

Stop Use And Ask A Veterinarian

If condition persists or increases, discontinue use and consult veterinarian.

Keep out of the reach of children.

If swallowed, get medical help or contact a Poison Control Center right away.

Directions

Pull down lower lid of the affected eye(s) and apply small amount (one-fourth inch) of ointment to the inside of the eyelid, one or more times daily, or as directed by a veterinarian.

Other Information

- Store at 20° to 25°C (68° to 77°F) [see USP controlled Room Temperature]
- Store away from heat
- Protect from freezing
- Keep tightly closed
- See crimp for Control Number and Expiration Date
- RETAIN THIS CARTON FOR FUTURE REFERENCE

Inactive Ingredient

Lanolin 2%

Principal Display Panel Text for Container Label:

NDC 46066-753-55

Pivetal™ Logo

ARTIFICIAL TEARS

Lubricant Ophthalmic Ointment FOR OPHTHALMC USE ONLY

For Veterinary Use Net Wt 3.5g (1/8 oz) Sterile

Principal Display Panel Text for Carton Label:

NDC 46066-753-55

Pivetal™ Logo

ARTIFICIAL TEARS

OINTMENT

Lubricant

Ophthalmic

Ointment

For Veterinary Use

STERILE

Net Wt 3.5 g (1/8 oz)